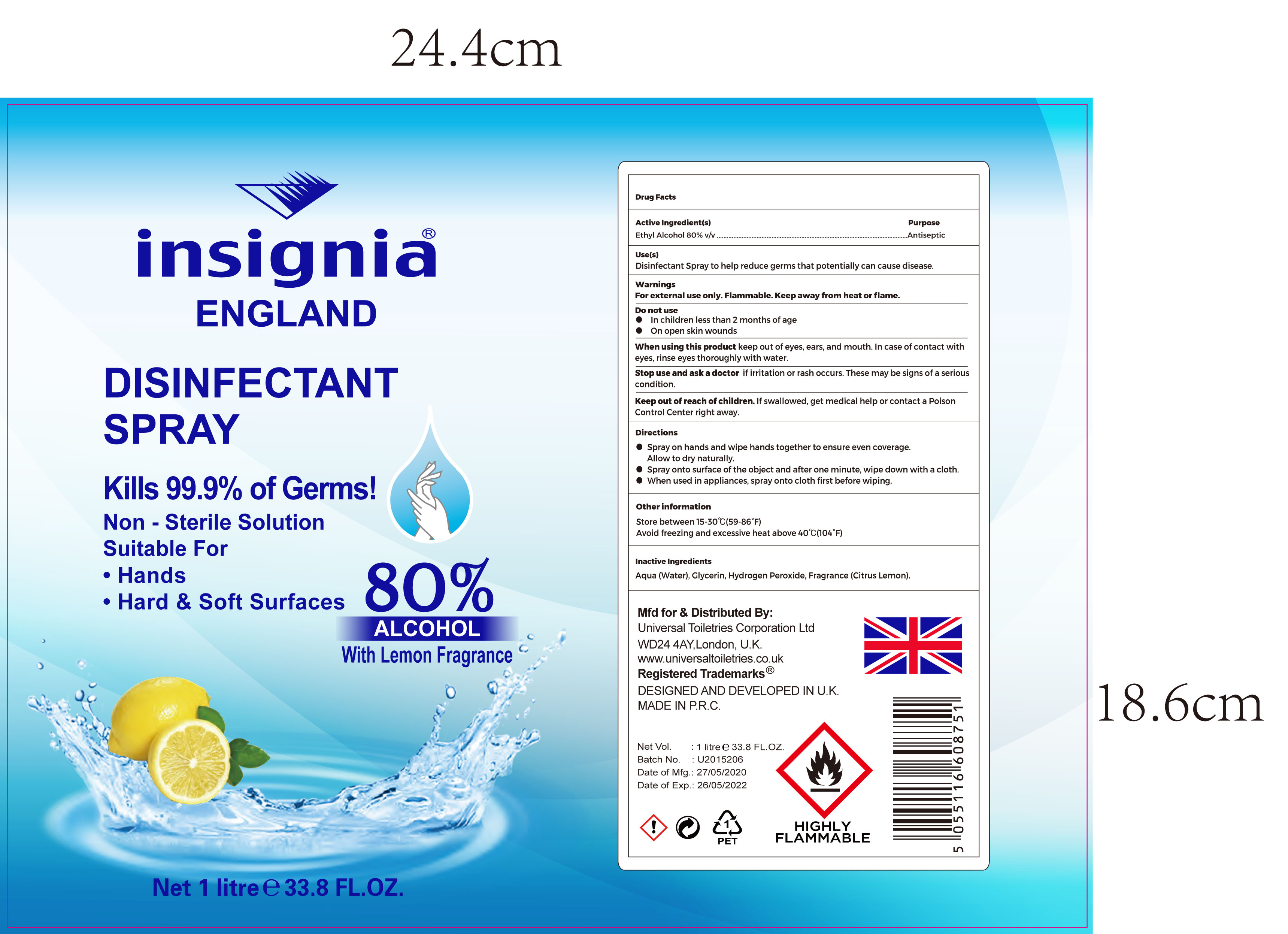 DRUG LABEL: Insignia England Disinfectant
NDC: 75410-004 | Form: SPRAY
Manufacturer: Yiwu Story of Love Cosmetic Co., Ltd
Category: otc | Type: HUMAN OTC DRUG LABEL
Date: 20200608

ACTIVE INGREDIENTS: ALCOHOL 80 mL/100 mL
INACTIVE INGREDIENTS: GLYCERIN; HYDROGEN PEROXIDE; CITRUS LIMON WHOLE

Active Ingredient(s)

Ethyl Alcohol 80% v/v

Purpose

Antiseptic

Use

Disinfectant Spray to help reduce germs that potentially can cause disease

Warnings

For external use only. Flammable. Keep away from heat or flame

Do not use in children

- less than 2 months of age
- on open skin wounds

Stop use and ask a doctor if irritation or rash occurs. This may be signs of serious condition

When using this product keep out of eyes, ears, and mouth. In case of contact with eyes, rinse eyes thoroughly with water.

Keep out of reach of children. If swallowed, get medical help or contact a Poison Control Center right away.

Directions

- Spray on hands and wipe hands together to ensure even coverage
- Allow to dry naturally
- Spray onto the surface of object and after one minute, wipe down with a cloth
- When used in appliances, spray onto cloth first before wiping

Other information

- Store between 15- 30C (59-86F)
- Avoid freezing and excessive heat above 40C (104F)

Inactive ingredients

Water, Glycerin, Hydrogen peroxide, Fragrance (Citrus lemon)